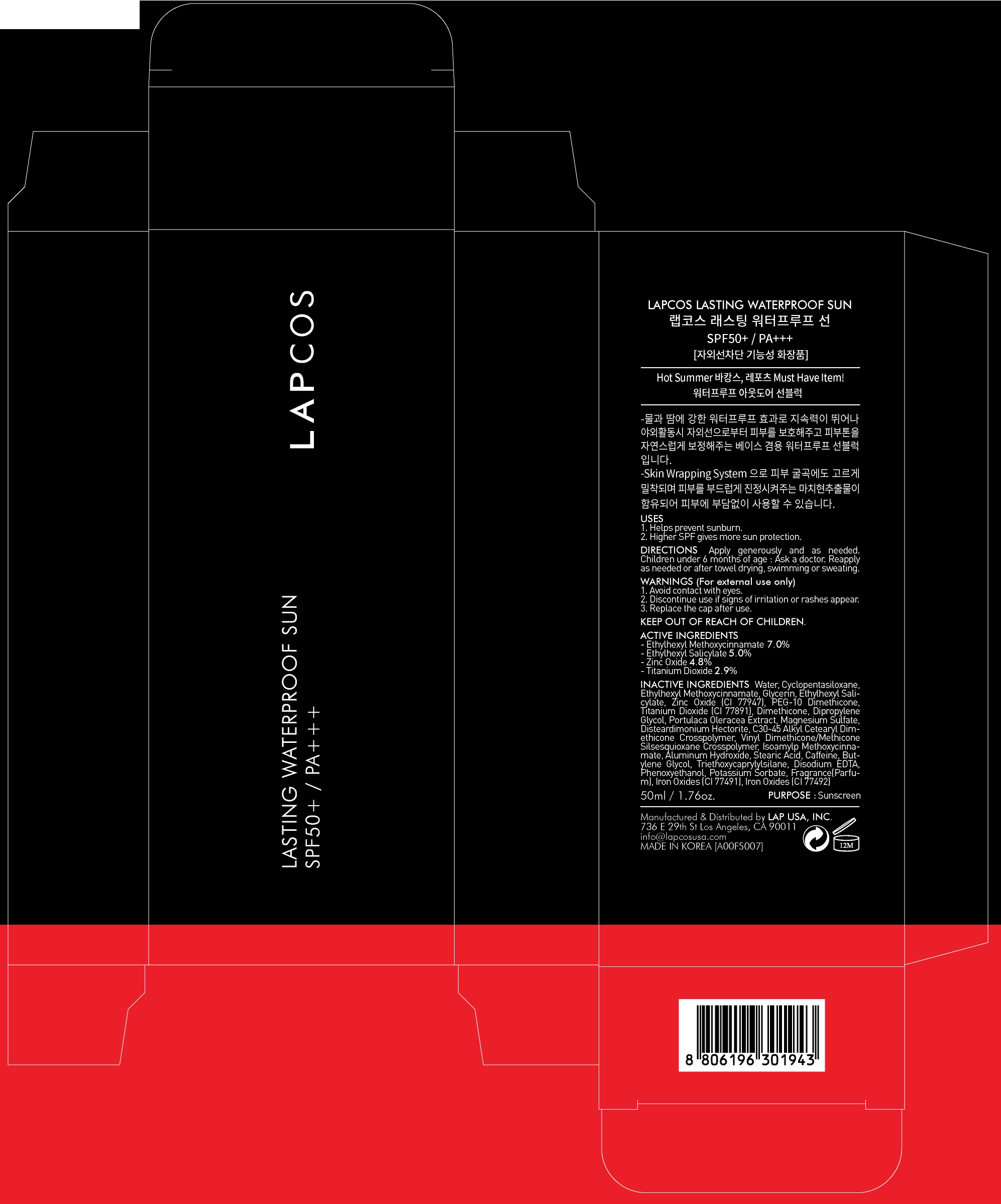 DRUG LABEL: LAPCOS Lasting Waterproof Sun
NDC: 71379-020 | Form: CREAM
Manufacturer: LAP CO.,LTD
Category: otc | Type: HUMAN OTC DRUG LABEL
Date: 20170504

ACTIVE INGREDIENTS: Octinoxate 3.50 g/50 mL; Octisalate 2.50 g/50 mL; Zinc Oxide 2.40 g/50 mL; Titanium Dioxide 1.45 g/50 mL
INACTIVE INGREDIENTS: Water; Dimethicone

ACTIVE INGREDIENT

Active ingredients: Ethylhexyl Methoxycinnamate 7.0%, Ethylhexyl Salicylate 5.0%, Zinc Oxide 4.8%, Titanium Dioxide 2.9%

INACTIVE INGREDIENT

Inactive ingredients: Water,Cyclopentasiloxane, PEG-10 Dimethicone, Dimethicone,Dipropylene Glycol,Portulaca Oleracea Extract,Magnesium Sulfate,Disteardimonium Hectorite,C30-45 Alkyl Cetearyl Dimethicone Crosspolymer,Vinyl Dimethicone/Methicone Silsesquioxane Crosspolymer,Isoamyl p-Methoxycinnamate,Aluminum Hydroxide,Stearic Acid,Caffeine,Butylene Glycol,Triethoxycaprylylsilane,Disodium EDTA,Phenoxyethanol,Potassium Sorbate,Fragrance(Parfum),Iron Oxides (CI 77491),Iron Oxides (CI 77492)

PURPOSE

Purpose: Sunscreen

WARNINGS

Warnings: For external use only Avoid contact with eyes. Discontinue use if signs of irritation or rashes appear. Replace the cap after use. Keep Out of Reach of Children

DESCRIPTION

Uses: - Helps prevent sunburn - Higher SPF gives more sun protection

Directions: - Apply generously and as needed. - Children under 6 months of age : Ask a doctor. - Reapply as needed or after towel drying, swimming or sweating.